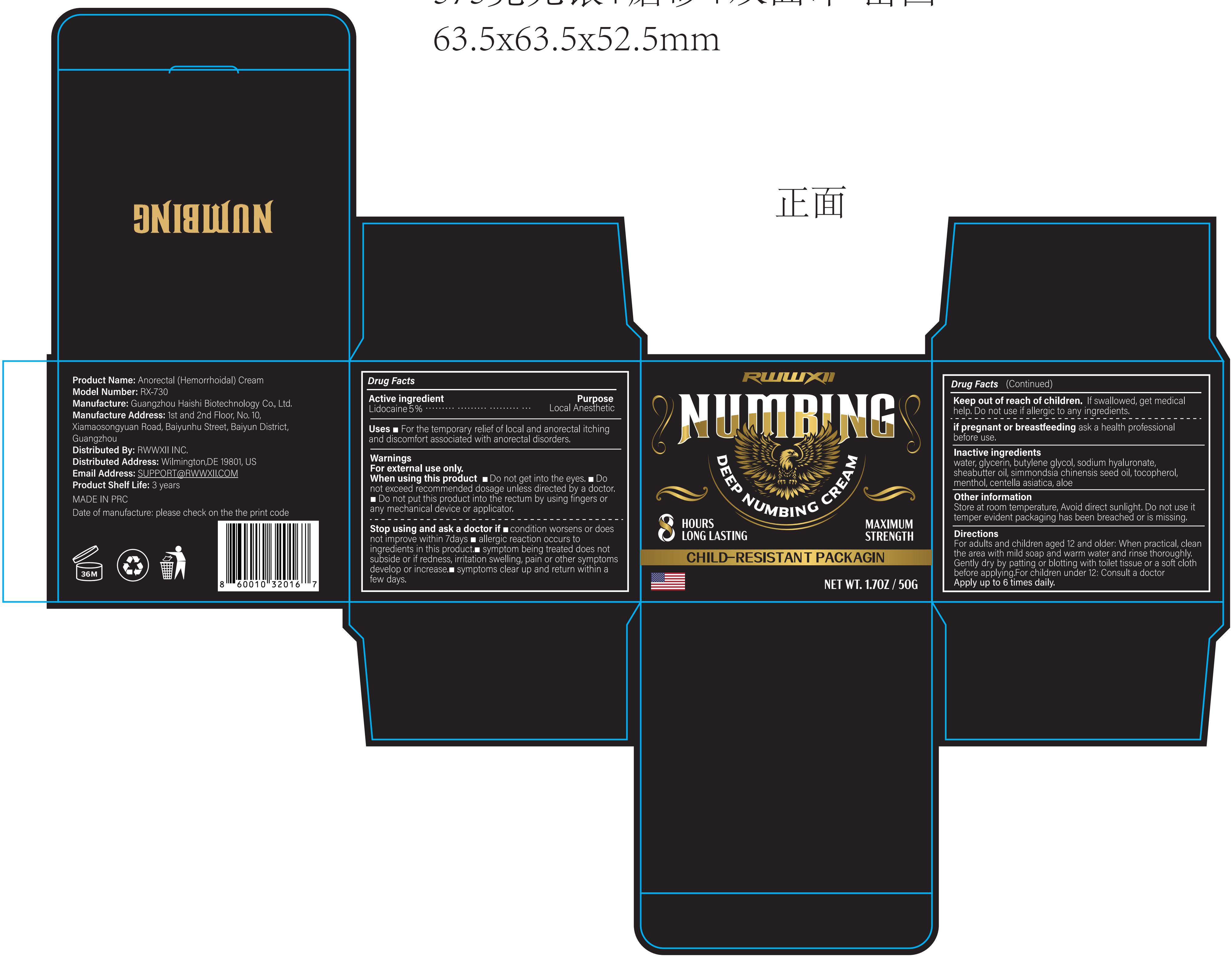 DRUG LABEL: RWWXII Deep Numbing Cream(Anorectal Hemorrhoidal Cream)
NDC: 60771-0027 | Form: CREAM
Manufacturer: Guangzhou Haishi Biological Technology Co., Ltd.
Category: otc | Type: HUMAN OTC DRUG LABEL
Date: 20250929

ACTIVE INGREDIENTS: LIDOCAINE 5 g/100 g
INACTIVE INGREDIENTS: GLYCERIN; BUTYLENE GLYCOL; SODIUM HYALURONATE; TOCOPHEROL; SHEA BUTTER; WATER; MENTHOL; ALOE; CENTELLA ASIATICA; SIMMONDSIA CHINENSIS (JOJOBA) SEED OIL

Active Ingredients

LIDOCAINE 5%

Purpose

For the temporary relief of local and anorectal itching and discomfort associated with anorectal disorders

Uses

For adults and children aged 12 and older: When practical, clean the area with mild soap and warm water and rinse thoroughly. Gently dry by patting or blotting with toilet tissue or a soft cloth before applying.
For children under 12: Consult a doctor

Warnings

For external use only

Stop Use

Stop use and ask a doctor if rash occurs.

Do Not Use

on damaged or broken skin.

When Using

When using this product keep out of eyes. Rinse with water to remove.

Keep Out Of Reach Of Children

If swallowed, get medical help or contact a Poison Control Center right away.

Dosage & administration

Squeeze out an appropriate amount of Numbing Cream and spread evenly on skin.

Inactive ingredients

WATER 65%
GLYCERIN 2%
BUTYLENE GLYCOL 5%
SODIUM HYALURONATE 0.1%
SHEABUTTER OIL 2%
SIMMONDSIA CHINENSIS SEED OIL 2%
TOCOPHEROL 0.5%
MENTHOL 2%
CENTELLA ASIATICA 0.5%
ALOE 0.5%